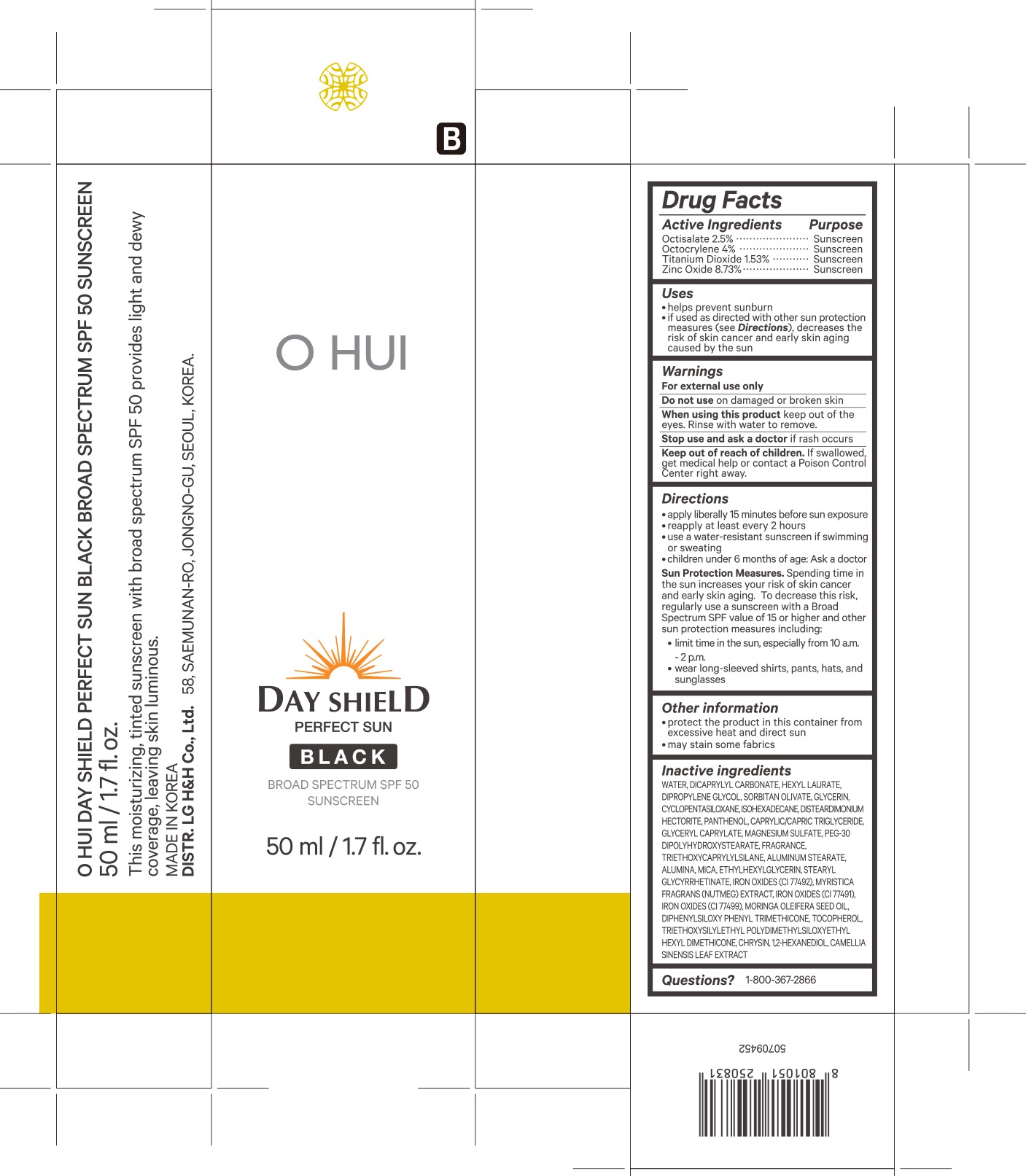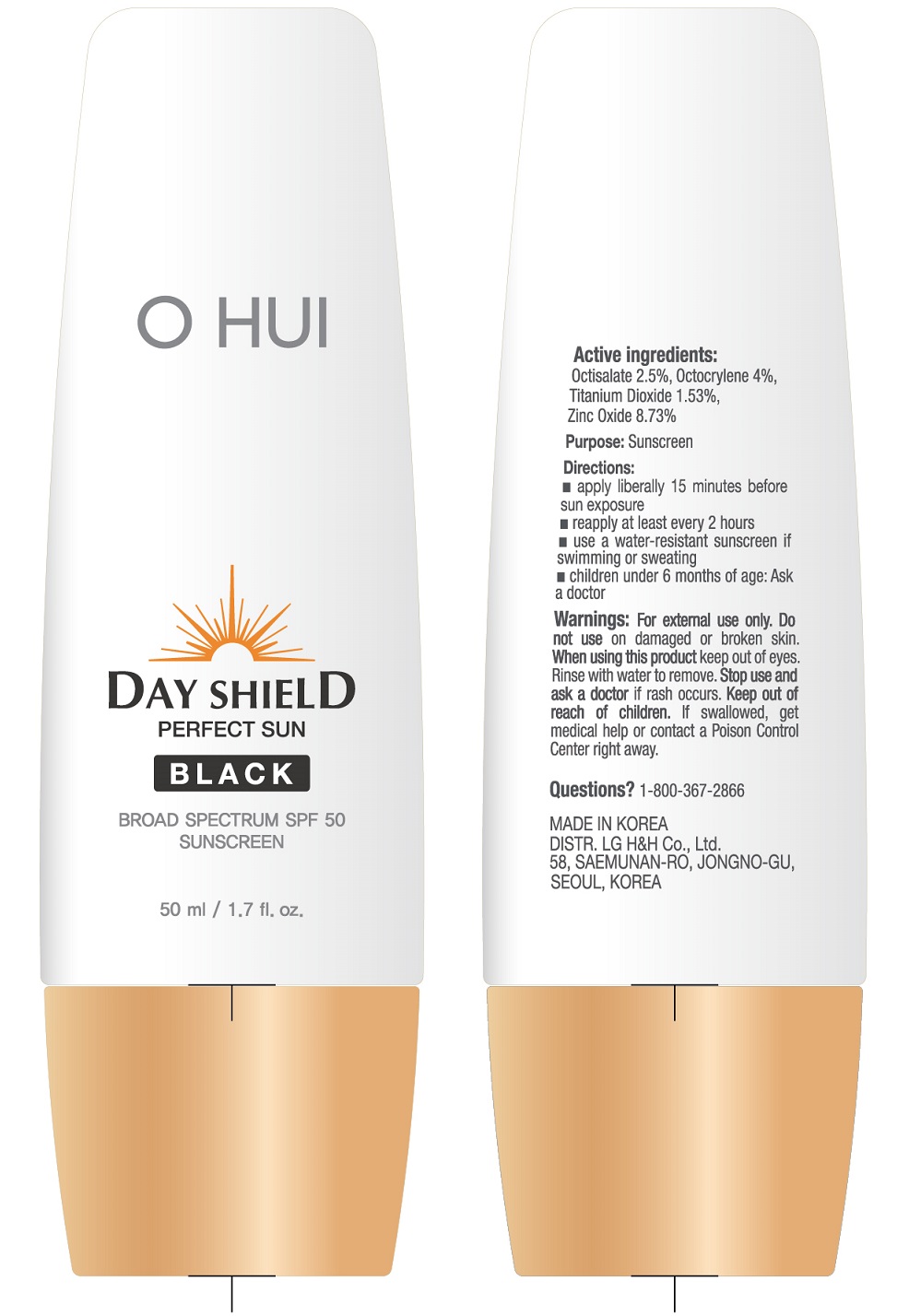 DRUG LABEL: O HUI DAY SHIELD PERFECT SUN BLACK BROAD SPECTRUM SPF 50 SUNSCREEN
NDC: 72330-650 | Form: CREAM
Manufacturer: fmg Co.Ltd
Category: otc | Type: HUMAN OTC DRUG LABEL
Date: 20250101

ACTIVE INGREDIENTS: OCTOCRYLENE 4 g/50 mL; ZINC OXIDE 8.73 g/50 mL; OCTISALATE 2.5 g/50 mL; TITANIUM DIOXIDE 1.53 g/50 mL
INACTIVE INGREDIENTS: WATER

72330-650-50 O HUI Day Shield Perfect Sun Black Broad Spectrum SPF 50 Sunscreen

Drug Facts

ACTIVE INGREDIENTS

Octisalate 2.5%

Octocrylene 4%

Titanium Dioxide 1.53%

Zinc Oxide 8.73%

PURPOSE

Sunscreen

USES

- helps prevent sunburn
- if used as directed with other sun protection measures (see Directions), decreases the risk of skin cancer and early skin aging caused by the sun

WARNINGS

For external use only

- Do not useon damaged or broken skin

WHEN USING

- When using this productkeep out of the eyes. Rinse with water to remove.

- Stop use and ask a doctorif rash occurs

- Keep out of reach of children.If swallowed, get medical help or contact a Poison Control Center right away.

DIRECTIONS

- apply liberally 15 minutes before sun exposure
- reapply at least every 2 hours
- use a water-resistant sunscreen if swimming or sweating
- children under 6 months of age: Ask a doctor
- Sun Protection Measures.Spending time in the sun increases your risk of skin cancer and early skin aging. To decrease this risk, regularly use a sunscreen with a Broad Spectrum SPF value of 15 or higher and other sun protection measures including:

- limit time in the sun, especially from 10 a.m.-2 p.m.
- wear long-sleeved shirts, pants, hats, and sunglasses

OTHER INFORMATION

- protect the product in this container from excessive heat and direct sun
- may stain some fabrics

INACTIVE INGREDIENTS

WATER, DICAPRYLYL CARBONATE, HEXYL LAURATE, DIPROPYLENE GLYCOL, SORBITAN OLIVATE, GLYCERIN, CYCLOPENTASILOXANE, ISOHEXADECANE, DISTEARDIMONIUM HECTORITE, PANTHENOL, CAPRYLIC/CAPRIC TRIGLYCERIDE, GLYCERYL CAPRYLATE, MAGNESIUM SULFATE, PEG-30 DIPOLYHYDROXYSTEARATE, FRAGRANCE, TRIETHOXYCAPRYLYLSILANE, ALUMINUM STEARATE, ALUMINA, MICA, ETHYLHEXYLGLYCERIN, STEARYL GLYCYRRHETINATE, IRON OXIDES(CI 77492), MYRISTICA FRAGRANS (NUTMEG) EXTRACT, IRON OXIDES(CI 77491), IRON OXIDES(CI 77499), MORINGA OLEIFERA SEED OIL, DIPHENYLSILOXY PHENYL TRIMETHICONE, TOCOPHEROL, TRIETHOXYSILYLETHYL POLYDIMETHYLSILOXYETHYL HEXYL DIMETHICONE, CHRYSIN, 1,2-HEXANEDIOL, CAMELLIA SINENSIS LEAF EXTRACT

QUESTIONS?

1-800-367-2866

This moisturizing, tinted sunscreen with broad spectrum SPF 50 provides light and dewy coverage, leaving skin luminous.

MADE IN KOREA

DISTR. LG H&H Co., Ltd. 58, SAEMUNAN-RO, JONGNO-GU, SEOUL, KOREA.

PRINCIPAL DISPLAY PANEL

O HUI

DAY SHIELD

PERFECT SUN

BLACK

BROAD SPECTRUM SPF 50
SUNSCREEN

50 ml / 1.7 fl. oz.